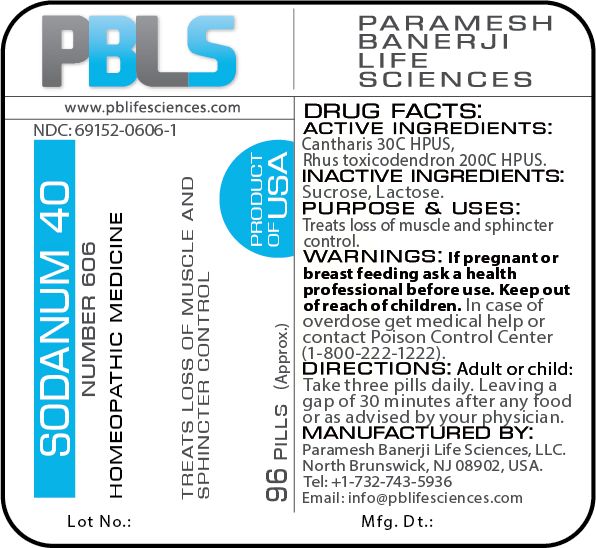 DRUG LABEL: Sodanum 40 (Number 606)
NDC: 69152-0606 | Form: PELLET
Manufacturer: Paramesh Banerji Life Sciences LLC
Category: homeopathic | Type: HUMAN OTC DRUG LABEL
Date: 20180702

ACTIVE INGREDIENTS: LYTTA VESICATORIA 30 [hp_C]/1 1; TOXICODENDRON PUBESCENS LEAF 200 [hp_C]/1 1
INACTIVE INGREDIENTS: SUCROSE; LACTOSE

DRUG FACTS: Active Ingredients

Cantharis 30C HPUS, Rhus toxicodendron 200C HPUS

Inactive Ingredients

Sucrose, Lactose

Purpose

Treats loss of muscle and sphincter control

Uses

Treats loss of muscle and sphincter control

Warnings

If pregnant or breast feeding ask a health professional before use.

Keep out of reach of children. In case of overdose, get medical help or contact a Poison Control Center (1-800-222-1222) right away.

Direction

Adult or child: Take three pills daily. Leaving a gap of 30 minutes after any food or as advised by your physician.

Manufactured by

Paramesh Banerji Life Sciences, LLC.

North Brunswick, NJ 08902, USA.

Tel: +1-732-743-5936

Email: info@pblifesciences.com

Principal Display Panel

NDC: 69152-0606-1

Sodanum 40

Number 606

Homeopathic Medicine

Treats loss of muscle and sphincter control

96 Pills (Approx.)

Product of USA